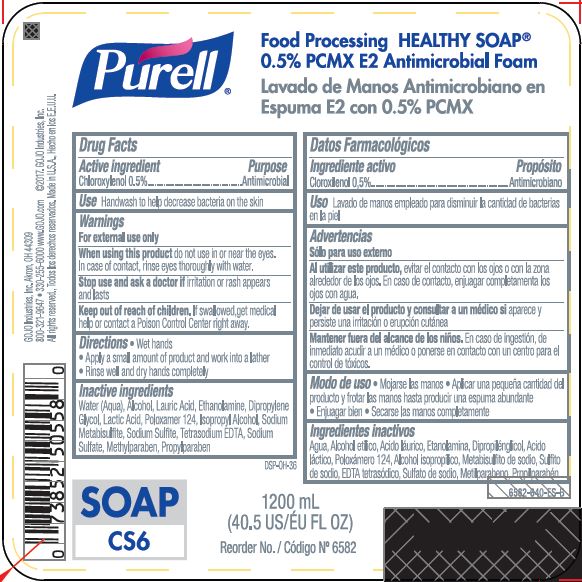 DRUG LABEL: PURELL Food Processing HEALTHY SP 0.5pct PCMX Antimicrobial E2 Foam Handwash
NDC: 21749-528 | Form: LIQUID
Manufacturer: GOJO Industries, Inc.
Category: otc | Type: HUMAN OTC DRUG LABEL
Date: 20251229

ACTIVE INGREDIENTS: CHLOROXYLENOL 0.005 mg/1 mL
INACTIVE INGREDIENTS: WATER; ALCOHOL; LAURIC ACID; MONOETHANOLAMINE; DIPROPYLENE GLYCOL; LACTIC ACID, UNSPECIFIED FORM; POLOXAMER 124; ISOPROPYL ALCOHOL; SODIUM METABISULFITE; SODIUM SULFITE; EDETATE SODIUM; SODIUM SULFATE; METHYLPARABEN; PROPYLPARABEN

PURELL Food Processing HEALTHY SOAP 0.5% PCMX Antimicrobial E2 Foam Handwash

Active ingredient

Chloroxylenol 0.5%

Purpose

Antimicrobial

Use

- Handwash to help decrease bacteria on the skin

Warnings

For external use only

WHEN USING

When using this productdo not use in or near the eyes. In case of contact, rinse eyes thoroughly with water.

Stop use and ask a doctor ifirritation or rash appears and lasts

Keep out of reach of children.If swallowed, get medical help or contact a Poison Control Center right away.

Directions

- Wet hands.
- Apply product and thoroughly cover hands with lather.
- Rinse well and dry hands completely.

Inactive ingredients

Water (Aqua), Alcohol, Lauric Acid, Ethanolamine, Dipropylene Glycol, Lactic Acid, Poloxamer 124, Isopropyl Alcohol, Sodium Metabisulfite, Sodium Sulfite, Tetrasodium EDTA, Sodium Sulfate, Methylparaben, Propylparaben